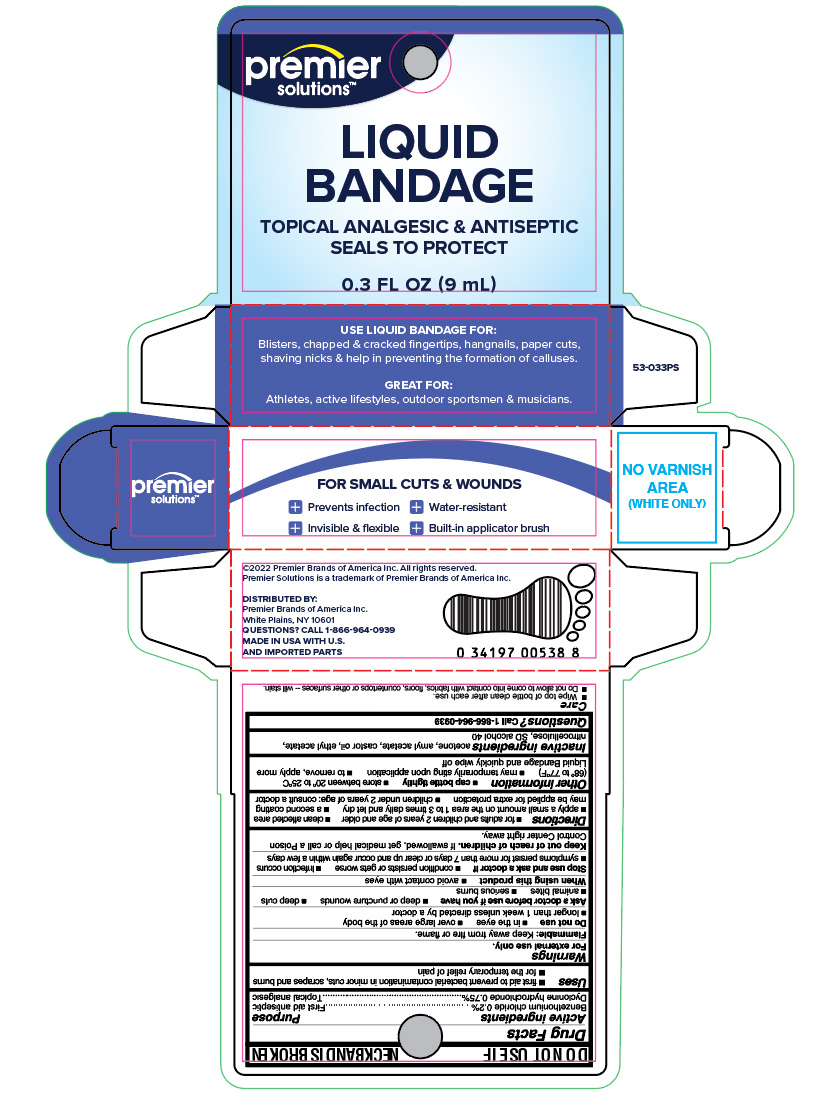 DRUG LABEL: Premier Solutions Liquid Bandage
NDC: 56104-246 | Form: LIQUID
Manufacturer: Premier Brands of America, Inc.
Category: otc | Type: HUMAN OTC DRUG LABEL
Date: 20251007

ACTIVE INGREDIENTS: BENZETHONIUM CHLORIDE 0.2 mg/10 mL; DYCLONINE HYDROCHLORIDE 0.75 mg/10 mL
INACTIVE INGREDIENTS: ACETONE; AMYL ACETATE; CASTOR OIL; ETHYL ACETATE; PYROXYLIN; ALCOHOL

Premier Solutions Liquid Bandage

Active ingredients

Benzethonium chloride 0.2%
Dyclonine hydrochloride 0.75%

Purpose

First aid antiseptic
Topical analgesic

Uses

- first aid to prevent bacteria contamination in minor cuts and scrapes

Warnings

For external use only.

Flammable:

do not use while smoking or near heat or flame.

Do not use

- in the eyes
- over large areas of the body
- longer than 1 week unless directed by a doctor
- on infected areas or wounds that are draining
- with other first aid products such as lotions and creams
- over sutures
- on mucous membranes

Ask a doctor before use if you have

- deep puncture wounds
- deep cuts
- animal bites
- serious burns

When using this product

Avoid contact with eyes

Stop use and ask a doctor if

- conditions persists or gets worse
- infection occurs
- symptoms persist for more than 7 days or clear up and occue again within a few days

Keep out of reach of children.

If swallowed, get medical help or call a Poison Control Center right away.

Directions

- For adults and children 2 years of age and older
- Clean affected area
- apply a small amount on the area 1-3 times daily let dry
- a second coating may be applied for extra protection
- children under 2 years of age: consult a doctor

Other information

- cap bottle tightly
- store between 20C to 25C (68F to 77F)
- may temporarily sting upon application
- to remove, apply more Liquid Bandage and quickly wipe off

Inactive ingredients

acetone, amyl acetate, castor oil, ethyl acetate, nitrocellulose, SD slcohol 40

Questions

Call 1-866-964-0939

Principal Display Panel

antiseptic
liquid
bandage
helps prevent infection
for small cuts and wounds
invisible, flexible, waterproof, easy to use

NET WT 0.3 FL OZ (9 mL)